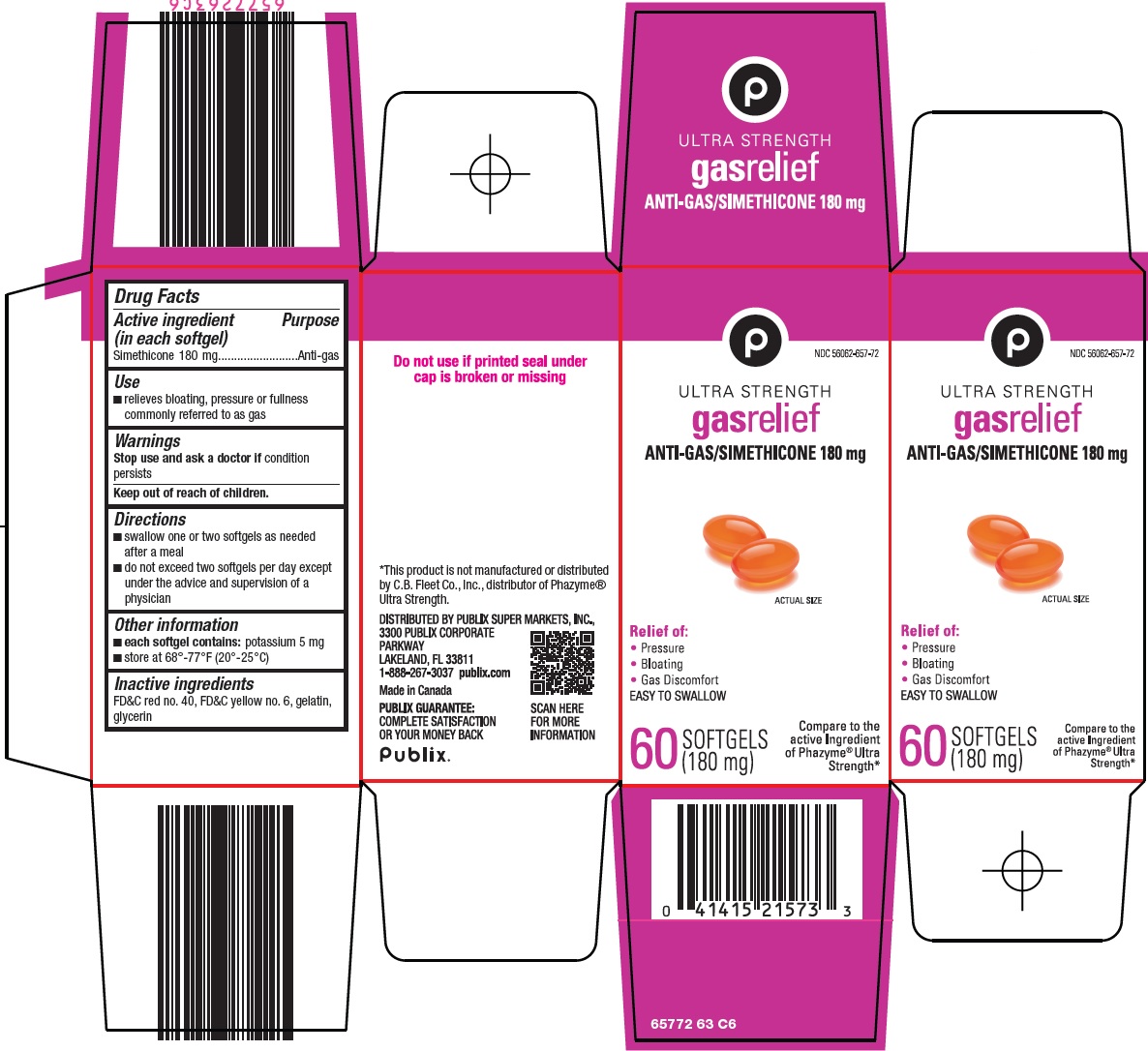 DRUG LABEL: Gas Relief
NDC: 56062-657 | Form: CAPSULE, LIQUID FILLED
Manufacturer: Publix Super Markets Inc
Category: otc | Type: HUMAN OTC DRUG LABEL
Date: 20240914

ACTIVE INGREDIENTS: DIMETHICONE 180 mg/1 1
INACTIVE INGREDIENTS: SILICON DIOXIDE; FD&C RED NO. 40; FD&C YELLOW NO. 6; GELATIN, UNSPECIFIED; GLYCERIN

Publix Super Markets, Inc. Gas Relief Drug Facts

Active ingredient (in each softgel)

Simethicone 180 mg

Purpose

Anti-gas

Use

- relieves bloating, pressure or fullness commonly referred to as gas

Warnings

Stop use and ask a doctor if

condition persists

Directions

- swallow one or two softgels as needed after a meal
- do not exceed two softgels per day except under the advice and supervision of a physician

Other information

- each softgel contains: potassium 5 mg
- store at 68°-77°F (20°-25°C)

Inactive ingredients

FD&C red no. 40, FD&C yellow no. 6, gelatin, glycerin

Principal Display Panel

P

ULTRA STRENGTH

gas relief

ANTI-GAS/SIMETHICONE 180 mg

ACTUAL SIZE

Relief of:

• Pressure

• Bloating

• Gas Discomfort

EASY TO SWALLOW

60 SOFTGELS (180 mg)

Compare to the active ingredient of Phazyme® Ultra Strength